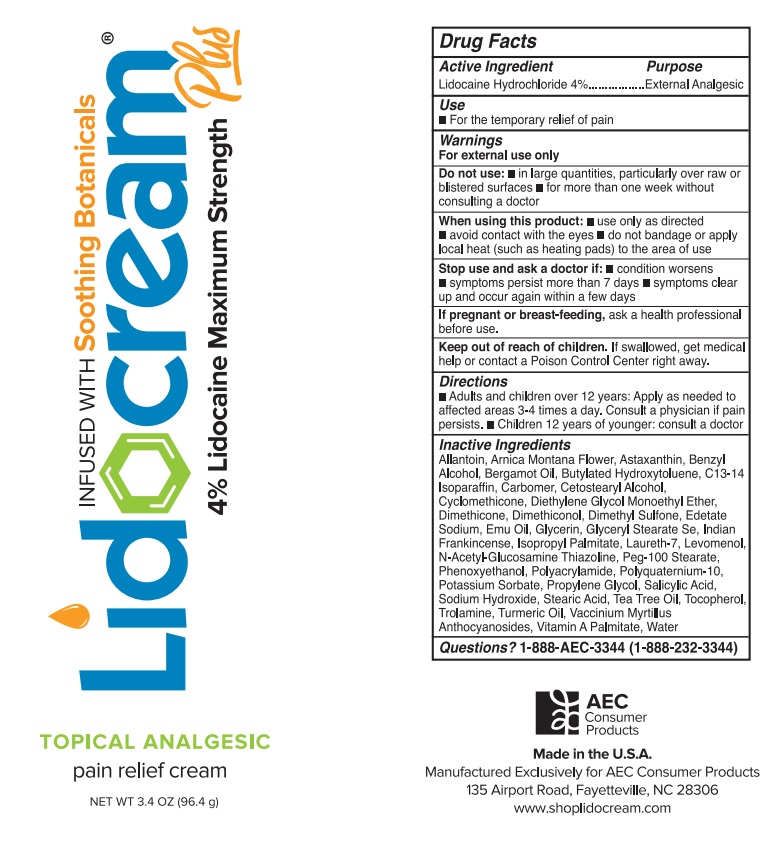 DRUG LABEL: Lidocream Plus
NDC: 86089-200 | Form: CREAM
Manufacturer: AEC Consumer Products, LLC
Category: otc | Type: HUMAN OTC DRUG LABEL
Date: 20220228

ACTIVE INGREDIENTS: LIDOCAINE HYDROCHLORIDE 4 g/100 g
INACTIVE INGREDIENTS: ALLANTOIN; ARNICA MONTANA FLOWER; ASTAXANTHIN; BENZYL ALCOHOL; BERGAMOT OIL; BUTYLATED HYDROXYTOLUENE; C13-14 ISOPARAFFIN; CARBOMER INTERPOLYMER TYPE B (ALLYL PENTAERYTHRITOL CROSSLINKED); CETOSTEARYL ALCOHOL; CYCLOMETHICONE; DIETHYLENE GLYCOL MONOETHYL ETHER; DIMETHICONE; DIMETHICONE 200; DIMETHYL SULFONE; EDETATE SODIUM; EMU OIL; GLYCERIN; GLYCERYL STEARATE SE; INDIAN FRANKINCENSE; ISOPROPYL PALMITATE; LAURETH-7; LEVOMENOL; N-ACETYL-GLUCOSAMINE THIAZOLINE; PEG-100 STEARATE; PHENOXYETHANOL; POLYACRYLAMIDE (10000 MW); POLYQUATERNIUM-10 (400 MPA.S AT 2%); POTASSIUM SORBATE; PROPYLENE GLYCOL; SALICYLIC ACID; SODIUM HYDROXIDE; STEARIC ACID; TEA TREE OIL; TOCOPHEROL; TROLAMINE; TURMERIC OIL; VACCINIUM MYRTILLUS ANTHOCYANOSIDES; VITAMIN A PALMITATE; WATER

Lidocream® Plus

Active Ingredient

Lidocaine Hydrochloride 4%

Purpose

External Analgesic

Use

• For the temporary relief of pain

Warnings

For external use only

Do not use: • in large quantities, particularly over raw or blistered surfaces • for more than one week without consulting a doctor

When using this product: • use only as directed • avoid contact with the eyes • do not bandage or apply local heat (such as heating pads) to the area of use

Stop use and ask a doctor if: • condition worsens • symptoms persist more than 7 days • symptoms clear up and occur again within a few days

If pregnant or breast-feeding, ask a health professional before use.

Keep out of reach of children. If swallowed, get medical help or contact a Poison Control Center right away.

Directions

• Adults and children over 12 years: Apply as needed to affected areas 3-4 times a day. Consult a physician if pain persists. • Children 12 years of younger: consult a doctor

Inactive Ingredients

Allantoin, Arnica Montana Flower, Astaxanthin, Benzyl Alcohol, Bergamot Oil, Butylated Hydroxytoluene, C13-14 Isoparaffin, Carbomer, Cetostearyl Alcohol, Cyclomethicone, Diethylene Glycol Monoethyl Ether, Dimethicone, Dimethiconol, Dimethyl Sulfone, Edetate Sodium, Emu Oil, Glycerin, Glyceryl Stearate Se, Indian Frankincense, Isopropyl Palmitate, Laureth-7, Levomenol, N-Acetyl-Glucosamine Thiazoline, Peg-100 Stearate, Phenoxyethanol, Polyacrylamide, Polyquaternium-10, Potassium Sorbate, Propylene Glycol, Salicylic Acid, Sodium Hydroxide, Stearic Acid, Tea Tree Oil, Tocopherol, Trolamine, Turmeric Oil, Vaccinium Myrtillus Anthocyanosides, Vitamin A Palmitate, Water

Questions?

1-888-AEC-3344 (1-888-232-3344)

ADVANCING PAIN RELIEF®

INFUSED WITH Soothing Botanicals

4% Lidocaine Maximum Strength

TOPICAL ANALGESIC

pain relief cream

AEC Consumer Products

Made in the U.S.A.

Manufactured Exclusively for AEC Consumer Products

135 Airport Road, Fayetteville, NC 28306

www.shoplidocream.com